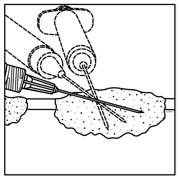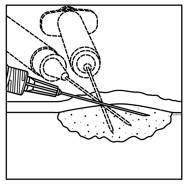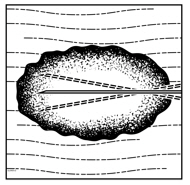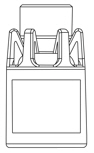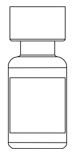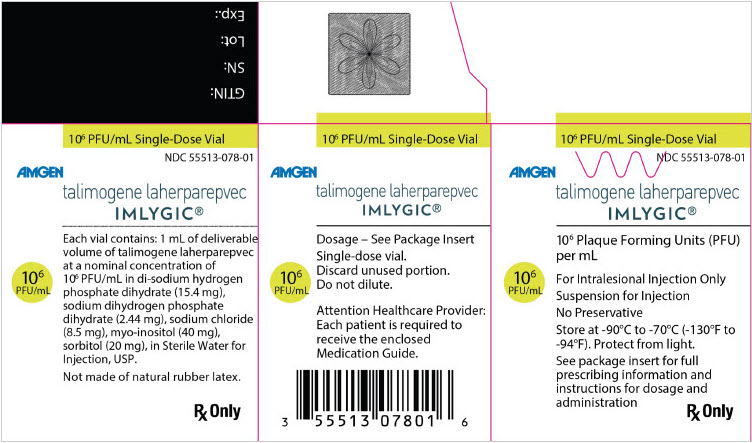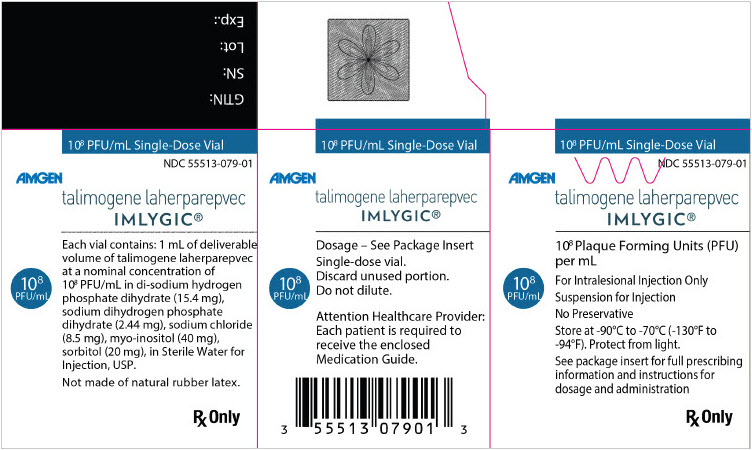 DRUG LABEL: Imlygic
NDC: 55513-078 | Form: INJECTION, SUSPENSION
Manufacturer: Amgen Inc
Category: prescription | Type: HUMAN PRESCRIPTION DRUG LABEL
Date: 20250404

ACTIVE INGREDIENTS: TALIMOGENE LAHERPAREPVEC 1000000 [PFU]/1 mL
INACTIVE INGREDIENTS: SODIUM PHOSPHATE, DIBASIC, DIHYDRATE 15.4 mg/1 mL; SODIUM PHOSPHATE, MONOBASIC, DIHYDRATE 2.44 mg/1 mL; SODIUM CHLORIDE 8.5 mg/1 mL; INOSITOL 40 mg/1 mL; SORBITOL 20 mg/1 mL; WATER

HIGHLIGHTS OF PRESCRIBING INFORMATION

These highlights do not include all the information needed to use IMLYGIC safely and effectively. See full prescribing information for IMLYGIC.
IMLYGIC® (talimogene laherparepvec)
Suspension for intralesional injection
Initial U.S. Approval: 2015

RECENT MAJOR CHANGES

Warnings and Precautions (5.2) | 2/2023
Warnings and Precautions (5.7) | 6/2022

1 INDICATIONS AND USAGE

IMLYGIC is a genetically modified oncolytic viral therapy indicated for the local treatment of unresectable cutaneous, subcutaneous, and nodal lesions in patients with melanoma recurrent after initial surgery.

Limitations of use: IMLYGIC has not been shown to improve overall survival or have an effect on visceral metastases. (1)

2 DOSAGE AND ADMINISTRATION

- Administer IMLYGIC by injection into cutaneous, subcutaneous, and/or nodal lesions. (2.1)
- Recommended starting dose is up to a maximum of 4 mL of IMLYGIC at a concentration of 10^6 (1 million) plaque-forming units (PFU) per mL. Subsequent doses should be administered up to 4 mL of IMLYGIC at a concentration of 10^8 (100 million) PFU per mL. (2.1)

3 DOSAGE FORMS AND STRENGTHS

Injection: 10^6 (1 million) PFU per mL, 10^8 (100 million) PFU per mL in single-dose vials (3)

4 CONTRAINDICATIONS

- Immunocompromised Patients (4.1)
- Pregnant Patients (4.2)

5 WARNINGS AND PRECAUTIONS

- Accidental Exposure to IMLYGIC: Accidental exposure may lead to transmission of IMLYGIC and herpetic infection. Healthcare providers and close contacts should avoid direct contact with injected lesions, dressings, or body fluids of treated patients.
  Accidental Exposure to IMLYGIC continued: Healthcare providers who are immunocompromised or pregnant should not prepare or administer IMLYGIC. If accidental exposure occurs, exposed individuals should clean the affected area. (5.1)
- Herpetic Infection: Patients who develop herpetic infections should be advised to follow standard hygienic practices to prevent viral transmission. (5.2)
- Injection Site Complications: Consider the risks and benefits before continuing IMLYGIC treatment if persistent infection or delayed healing develops. (5.3)
- Immune-Mediated Events: Consider the risks and benefits of IMLYGIC before initiating treatment in patients who have underlying autoimmune disease or before continuing treatment in patients who develop immune-mediated events. (5.4)
- Plasmacytoma at the Injection Site: Consider the risks and benefits in patients with multiple myeloma or in whom plasmacytoma develops during treatment. (5.5)
- Obstructive Airway Disorder: Use caution when injecting lesions close to major airways. (5.6)
- Hepatic Hemorrhage from Transcutaneous Intrahepatic Route of Administration: IMLYGIC is not indicated for treatment via transcutaneous intrahepatic route of administration. (5.7)

6 ADVERSE REACTIONS

The most commonly reported adverse drug reactions (≥ 25%) in IMLYGIC-treated patients were fatigue, chills, pyrexia, nausea, influenza-like illness, and injection site pain. (6)

To report SUSPECTED ADVERSE REACTIONS, contact Amgen at 1-855-IMLYGIC (1-855-465-9442) or FDA at 1-800-FDA-1088 or www.fda.gov/medwatch.

8 USE IN SPECIFIC POPULATIONS

- Pregnancy: Women of childbearing potential should be advised to use an effective method of contraception to prevent pregnancy during treatment with IMLYGIC. (8.1)
- Lactation: Discontinue drug or nursing. (8.2)

FULL PRESCRIBING INFORMATION

1 INDICATIONS AND USAGE

IMLYGIC is a genetically modified oncolytic viral therapy indicated for the local treatment of unresectable cutaneous, subcutaneous, and nodal lesions in patients with melanoma recurrent after initial surgery.

Limitations of use: IMLYGIC has not been shown to improve overall survival or have an effect on visceral metastases.

2 DOSAGE AND ADMINISTRATION

For intralesional injection only. Do not administer intravenously.

2.1 Dose

Administer IMLYGIC by injection into cutaneous, subcutaneous, and/or nodal lesions that are visible, palpable, or detectable by ultrasound guidance.

IMLYGIC is provided in single-dose vials of 1 mL each in two different dose strengths:

- 10^6 (1 million) plaque-forming units (PFU) per mL (light green cap) – for initial dose only
- 10^8 (100 million) PFU per mL (royal blue cap) – for all subsequent doses

Recommended Dose and Schedule

The total injection volume for each treatment visit should not exceed 4 mL for all injected lesions combined. It may not be possible to inject all lesions at each treatment visit or over the full course of treatment. Previously injected and/or uninjected lesion(s) may be injected at subsequent treatment visits. The initial recommended dose is up to 4 mL of IMLYGIC at a concentration of 10^6 (1 million) PFU per mL. The recommended dose for subsequent administrations is up to 4 mL of IMLYGIC at a concentration of 10^8 (100 million) PFU per mL. The recommended dosing schedule for IMLYGIC is shown in Table 1.

Table 1. Recommended Dose and Schedule for IMLYGIC
Treatment | Treatment Interval | Maximum Injection Volume per Treatment Visit (all lesions combined) | Dose Strength | Prioritization of Lesions to be Injected
Initial | – | 4 mL | 10^6 (1 million) PFU per mL | - Inject largest lesion(s) first. - Prioritize injection of remaining lesion(s) based on lesion size until maximum injection volume is reached or until all injectable lesion(s) have been treated.
Second | 3 weeks after initial treatment | 4 mL | 10^8 (100 million) PFU per mL | - Inject any new lesion(s) (lesions that have developed since initial treatment) first. - Prioritize injection of remaining lesion(s) based on lesion size until maximum injection volume is reached or until all injectable lesion(s) have been treated.
All subsequent treatments (including reinitiation) | 2 weeks after previous treatment | 4 mL | 10^8 (100 million) PFU per mL | - Inject any new lesion(s) (lesions that have developed since previous treatment) first. - Prioritize injection of remaining lesion(s) based on lesion size until maximum injection volume is reached or until all injectable lesion(s) have been treated.

Dose Volume Determination (per Lesion)

Use Table 2 to determine the volume of IMLYGIC injection for each lesion.

Table 2. Determination of IMLYGIC Injection Volume Based on Lesion Size
Lesion Size (longest dimension) | Injection Volume
> 5 cm | up to 4 mL
> 2.5 cm to 5 cm | up to 2 mL
> 1.5 cm to 2.5 cm | up to 1 mL
> 0.5 cm to 1.5 cm | up to 0.5 mL
≤ 0.5 cm | up to 0.1 mL

When lesions are clustered together, inject them as a single lesion according to Table 2.

Continue IMLYGIC treatment for at least 6 months unless other treatment is required or until there are no injectable lesions to treat.

Reinitiate IMLYGIC treatment if new unresectable cutaneous, subcutaneous, or nodal lesions appear after a complete response.

2.2 Preparation and Handling

Healthcare providers who are immunocompromised or pregnant should not prepare or administer IMLYGIC and should not come into direct contact with the IMLYGIC injection sites, dressings, or body fluids of treated patients [see Warnings and Precautions (5.1)].

Avoid accidental exposure to IMLYGIC and follow below instructions for preparation, administration, and handling of IMLYGIC:

- Wear personal protective equipment (protective gown or laboratory coat, safety glasses or face shield, and gloves) while preparing or administering IMLYGIC.
- Avoid accidental exposure to IMLYGIC, especially contact with skin, eyes, and mucous membranes.
  ○ Cover any exposed wounds before handling.
  ○ In the event of an accidental occupational exposure (e.g., through a splash to the eyes or mucous membranes), flush with clean water for at least 15 minutes.
  ○ In the event of exposure to broken skin or needle stick, clean the affected area thoroughly with soap and water and/or a disinfectant.
- Clean all surfaces that may have come in contact with IMLYGIC and treat all IMLYGIC spills with a virucidal agent such as 1% sodium hypochlorite or 70% isopropyl alcohol and blot using absorbent materials.
- Dispose of all materials that may have come in contact with IMLYGIC (e.g., vial, syringe, needle, cotton gauze, gloves, masks, or dressings) as biohazardous waste.
- Advise patients to place used dressings and cleaning materials into a sealed plastic bag and dispose in household waste.

Thawing IMLYGIC Vials

1. Determine the total volume required for injection, up to 4 mL [see Dosage and Administration (2.1)].
2. Thaw frozen IMLYGIC vials at room temperature [20°C to 25°C (68°F to 77°F)] until IMLYGIC is liquid. The time to achieve complete vial thaw is expected to be 30 to 70 minutes, depending on the ambient temperature. Do not expose the vial to higher temperatures. Keep the vial in original carton during thawing.
3. Swirl gently. Do NOT shake.
4. After thawing, administer IMLYGIC immediately or store in its original vial and carton, as follows:
  - Thawed IMLYGIC is stable when stored at temperatures of 2°C (36°F) up to 25°C (77°F) protected from light in its original vial and carton for the storage times specified in Table 3. Do not exceed the storage times specified in Table 3.
  - IMLYGIC must not be refrozen once it is thawed. Discard any thawed IMLYGIC in the vial stored longer than the specified times in Table 3.

Table 3. Maximum Storage Time for Thawed Imlygic in Vial
 | 10^6 (1 million) PFU/mL | 10^8 (100 million) PFU/mL
2°C to 8°C (36°F to 46°F) | 24 hours | 1 week (7 days)
up to 25°C (77°F) | 12 hours | 24 hours

5. Prepare sterile syringes and needles. A detachable 18-26 G needle or nondetachable 22-26 G staked needle (which minimizes hold up volume) may be used for IMLYGIC withdrawal and a detachable or nondetachable staked needle of 22–26 G may be used for injection. Small unit syringes (e.g., 0.5 mL insulin syringes) are recommended for better injection control.
6. Using aseptic technique, remove the vial cap and withdraw the product from the vial into the syringe(s), noting the total volume. Avoid generating aerosols when loading syringes with product and use a biologic safety cabinet if available.

2.3 Administration

Follow the steps below to administer IMLYGIC to patients:

Pre-Injection

1. Clean the lesion and surrounding areas with an alcohol swab and let dry.
2. Treat the injection site with a topical or local anesthetic agent, if necessary. Do not inject anesthetic agent directly into the lesion. Inject anesthetic agent around the periphery of the lesion.

Injection

1. Inject IMLYGIC intralesionally into cutaneous, subcutaneous, and/or nodal lesions that are visible, palpable, or detectable by ultrasound guidance. Using a single insertion point, inject IMLYGIC along multiple tracks as far as the radial reach of the needle allows within the lesion to achieve even and complete dispersion. Multiple insertion points may be used if a lesion is larger than the radial reach of the needle.
  Figure 1: Injection administration for cutaneous lesions
  Figure 2: Injection administration for subcutaneous lesions
  Figure 3: Injection administration for nodal lesions
2. Inject IMLYGIC evenly and completely within the lesion by pulling the needle back without exiting the lesion. Redirect the needle as many times as necessary while injecting the remainder of the dose of IMLYGIC. Continue until the full dose is evenly and completely dispersed.
3. When removing the needle, withdraw it from the lesion slowly to avoid leakage of IMLYGIC at the insertion point.
4. Repeat steps 1-2 under pre-injection and steps 1-3 under injection for other lesions to be injected.
5. Use a new needle any time the needle is completely removed from a lesion and each time a different lesion is injected.

Post-Injection

1. Apply pressure to the injection site(s) with sterile gauze for at least 30 seconds.
2. Swab the injection site(s) and surrounding area with alcohol.
3. Change gloves and cover the injected lesion(s) with an absorbent pad and dry occlusive dressing.
4. Wipe the exterior of occlusive dressing with alcohol.
5. Advise patients to:
  - Keep the injection site(s) covered for at least the first week after each treatment visit or longer if the injection site is weeping or oozing.
  - Replace the dressing if it falls off.

3 DOSAGE FORMS AND STRENGTHS

- Initial dose only: 10^6 (1 million) PFU per mL solution in 1 mL single-dose vial (light green cap)
- Subsequent doses: 10^8 (100 million) PFU per mL solution in 1 mL single-dose vial (royal blue cap)

4 CONTRAINDICATIONS

4.1 Immunocompromised Patients

IMLYGIC is a live, attenuated herpes simplex virus and may cause life-threatening disseminated herpetic infection in patients who are immunocompromised. Do not administer IMLYGIC to immunocompromised patients, including those with a history of primary or acquired immunodeficient states, leukemia, lymphoma, AIDS or other clinical manifestations of infection with human immunodeficiency viruses, and those on immunosuppressive therapy [see Nonclinical Toxicology (13.2)].

4.2 Pregnant Patients

Do not administer IMLYGIC to pregnant patients.

5 WARNINGS AND PRECAUTIONS

5.1 Accidental Exposure to IMLYGIC

Accidental exposure may lead to transmission of IMLYGIC and herpetic infection. Accidental needle stick and splashback to the eyes have been reported in healthcare providers during preparation and administration of IMLYGIC.

Healthcare providers, close contacts (household members, caregivers, sex partners, or persons sharing the same bed), pregnant women, and newborns should avoid direct contact with injected lesions, dressings, or body fluids of treated patients [see Dosage and Administration (2.2)]. Healthcare providers who are immunocompromised or pregnant should not prepare or administer IMLYGIC.

Caregivers should wear protective gloves when assisting patients in applying or changing occlusive dressings and observe safety precautions for disposal of used dressings, gloves, and cleaning materials [see Dosage and Administration (2.2)].

In the event of an accidental exposure to IMLYGIC, exposed individuals should clean the affected area thoroughly with soap and water and/or a disinfectant. If signs or symptoms of herpetic infection develop, the exposed individuals should contact their healthcare provider for appropriate treatment [see Warnings and Precautions (5.2)].

Patients should avoid touching or scratching injection sites or their occlusive dressings, as doing so could lead to inadvertent transfer of IMLYGIC to other areas of the body.

5.2 Herpetic Infection

Herpetic infections (including but not limited to cold sores and herpetic keratitis) and serious cases of disseminated herpetic infections have been reported in patients treated with IMLYGIC, including fatal disseminated herpetic infection in the immunocompromised patient population [see Clinical Trials Experience (6.1) and Postmarketing Experience (6.2)]. Immunocompromised patients may be at increased risk of life-threatening disseminated herpetic infection [see Contraindications (4.1)].

Patients who develop suspicious herpes-like lesions should follow standard hygienic practices to prevent viral transmission. Patients or close contacts with suspected herpetic infections should also contact their healthcare provider to evaluate the lesions. Suspected herpetic lesions should be reported to Amgen at 1-855-IMLYGIC (1-855-465-9442); patients or close contacts have the option of follow-up testing for further characterization of the infection.

IMLYGIC is sensitive to acyclovir. Acyclovir or other antiviral agents may interfere with the effectiveness of IMLYGIC. Therefore, consider the risks and benefits of IMLYGIC treatment before administering antiviral agents to manage herpetic infection.

5.3 Injection Site Complications

Necrosis or ulceration of tumor tissue may occur during IMLYGIC treatment. Cellulitis and systemic bacterial infection have been reported in clinical studies. Careful wound care and infection precautions are recommended, particularly if tissue necrosis results in open wounds.

In clinical studies, impaired healing at the injection site has been reported. IMLYGIC may increase the risk of impaired healing in patients with underlying risk factors (e.g., previous radiation at the injection site or lesions in poorly vascularized areas). One patient had an amputation of a lower extremity 6 months after IMLYGIC injection due to an infected non-healing wound. This wound area had been treated with surgery and radiation prior to IMLYGIC treatment and had previous wound complications.

If there is persistent infection or delayed healing of the injection site(s), consider the risks and benefits of IMLYGIC before continuing treatment with IMLYGIC.

5.4 Immune-Mediated Events

IMLYGIC may result in immune-mediated events. In clinical studies, immune-mediated events, including glomerulonephritis, vasculitis, pneumonitis, worsening psoriasis, and vitiligo have been reported in patients treated with IMLYGIC.

Consider the risks and benefits of IMLYGIC before initiating treatment in patients who have underlying autoimmune disease or before continuing treatment in patients who develop immune-mediated events.

5.5 Plasmacytoma at the Injection Site

In a clinical study, a plasmacytoma has been reported in proximity to the injection site after administration of IMLYGIC in a patient with smoldering multiple myeloma.

Consider the risks and benefits of IMLYGIC in patients with multiple myeloma or in whom plasmacytoma develops during treatment.

5.6 Obstructive Airway Disorder

Obstructive airway disorder has been reported following IMLYGIC treatment. Use caution when injecting lesions close to major airways.

5.7 Hepatic Hemorrhage from Transcutaneous Intrahepatic Route of Administration

IMLYGIC is not indicated for transcutaneous intrahepatic route of administration. In clinical studies, cases of hepatic hemorrhage resulting in hospitalization and death have been reported in patients receiving transcutaneous intrahepatic IMLYGIC injections.

6 ADVERSE REACTIONS

The most commonly reported adverse drug reactions (≥ 25%) in IMLYGIC-treated patients were fatigue, chills, pyrexia, nausea, influenza-like illness, and injection site pain.

The following adverse reactions are discussed in greater detail in another section of the label:

- Herpetic Infection [see Warnings and Precautions (5.2)]
- Injection Site Complications [see Warnings and Precautions (5.3)]

6.1 Clinical Trials Experience

Because clinical trials are conducted under widely varying conditions, adverse reaction rates observed in the clinical trials of a drug cannot be directly compared to rates in the clinical trials of another drug and may not reflect the rates observed in practice.

The safety of IMLYGIC was evaluated in 419 patients who received at least 1 dose of either IMLYGIC (n = 292) or subcutaneously administered granulocyte-macrophage colony-stimulating factor (GM-CSF) (n = 127) in an open-label, randomized clinical study of patients with stage IIIB, IIIC, and IV melanoma that was not considered to be surgically resectable [see Clinical Studies (14)]. The median duration of exposure to IMLYGIC was 23 weeks (5.3 months). Twenty-six patients were exposed to IMLYGIC for at least 1 year.

Most adverse reactions reported were mild or moderate in severity and generally resolved within 72 hours. The most common grade 3 or higher adverse reaction was cellulitis [see Warnings and Precautions (5.3)].

Pyrexia, chills, and influenza-like illness can occur any time during IMLYGIC treatment but were more frequent during the first 3 months of treatment.

Table 4 below lists adverse reactions with a 5% or greater incidence in the IMLYGIC arm compared to the GM-CSF arm in the clinical study [see Clinical Studies (14)].

Table 4. Adverse Reactions Reported with At Least a 5% Greater Incidence in Patients Treated with IMLYGIC Compared to GM-CSF
Adverse Reactions | IMLYGIC (n = 292) |  | GM-CSF (n = 127)
 | Any Grade n (%) | Grade 3 n (%) | Any Grade n (%) | Grade 3 n (%)
General disorders and administration site conditions
Fatigue | 147 (50.3) | 6 (2.1) | 46 (36.2) | 1 (< 1)
Chills | 142 (48.6) |  | 11 (8.7)
Pyrexia | 125 (42.8) |  | 11 (8.7)
Influenza-like illness | 89 (30.5) | 2 (< 1) | 19 (15.0)
Injection site pain | 81 (27.7) | 2 (< 1) | 8 (6.3)
Gastrointestinal disorders
Nausea | 104 (35.6) | 1 (< 1) | 25 (19.7)
Vomiting | 62 (21.2) | 5 (1.7) | 12 (9.5)
Diarrhea | 55 (18.8) | 1 (< 1) | 14 (11.0)
Constipation | 34 (11.6) |  | 8 (6.3) | 1 (< 1)
Abdominal pain | 26 (8.9) | 2 (< 1) | 3 (2.4)
Musculoskeletal and connective tissue disorders
Myalgia | 51 (17.5) | 1 (< 1) | 7 (5.5)
Arthralgia | 50 (17.1) | 2 (< 1) | 11 (8.7)
Pain in extremity | 48 (16.4) | 4 (1.4) | 12 (9.5) | 1 (< 1)
Nervous system disorders
Headache | 55 (18.8) | 2 (< 1) | 12 (9.5)
Dizziness | 28 (9.6) |  | 4 (3.2)
Respiratory, thoracic, and mediastinal disorders
Oropharyngeal pain | 17 (5.8) |  | 1 (< 1)
Investigations
Weight decreased | 17 (5.8) | 1 (< 1) | 1 (< 1)

Other adverse reactions associated with IMLYGIC in the open-label, randomized study include rash, dermatitis, glomerulonephritis, vitiligo, worsening psoriasis, cellulitis, pneumonitis, vasculitis, herpetic keratitis, obstructive airway disorder, plasmacytoma at the injection site, deep vein thrombosis, and oral herpes.

6.2 Postmarketing Experience

The following adverse reactions have been identified during postapproval use of IMLYGIC. Because these reactions are reported voluntarily from a population of uncertain size, it is not always possible to reliably estimate their frequency or establish a causal relationship to drug exposure.

- Herpetic infections including disseminated herpetic infections [see Warnings and Precautions (5.2)]. Serious including fatal disseminated herpetic infections in immunocompromised patient population [see Contraindications (4.1) and Warnings and Precautions (5.2)].

7 DRUG INTERACTIONS

IMLYGIC is sensitive to acyclovir. Acyclovir or other antiherpetic viral agents may interfere with the effectiveness of IMLYGIC. No drug interaction studies have been conducted with IMLYGIC.

8 USE IN SPECIFIC POPULATIONS

8.1 Pregnancy

Risk Summary

Adequate and well-controlled studies with IMLYGIC have not been conducted in pregnant women. No effects on embryo-fetal development have been observed in a study conducted in pregnant mice. The design of the study limits application of the animal data to humans [see Data].

In the U.S. general population, the estimated background risk of major birth defects and miscarriage in clinically recognized pregnancies is 2-4% and 15-20%, respectively.

Clinical Considerations

If the patient becomes pregnant while taking IMLYGIC, the patient should be apprised of the potential hazards to the fetus and neonate. Women of childbearing potential should be advised to use an effective method of contraception to prevent pregnancy during treatment with IMLYGIC.

If a pregnant woman has an infection with wild-type Herpes Simplex Virus Type 1 (HSV-1) (primary or reactivation), there is potential for the virus to cross the placental barrier and also a risk of transmission during birth due to viral shedding. Infections with wild-type HSV-1 have been associated with serious adverse effects, including multi-organ failure and death, if a fetus or neonate contracts the wild-type herpes infection. While there are no clinical data to date on IMLYGIC infections in pregnant women, there could be a risk to the fetus or neonate if IMLYGIC were to act in the same manner.

Data

Animal Data

No effects on embryo-fetal development were observed when IMLYGIC was intravenously administered during organogenesis to immunocompetent pregnant mice at doses up to 4 x 10^8 (400 million) PFU per kg (60-fold higher, on a PFU per kg basis, compared to the maximum clinical dose). Levels of IMLYGIC DNA in pooled fetal blood were at or below the assay detection level. Study design limitations included: 1) administration of IMLYGIC expressing human granulocyte-macrophage colony-stimulating factor (huGM-CSF), which is not biologically active in mice; 2) unknown transplacental kinetics of IMLYGIC following intravenous administration in pregnant mice; and 3) unknown significance of IMLYGIC dose extrapolation from animal to human based on body weight.

8.2 Lactation

Risk Summary

There is no information regarding the presence of IMLYGIC in human milk, the effects on the breastfed infant, or the effects on milk production. The developmental and health benefits of breastfeeding should be considered along with the mother's clinical need for IMLYGIC and any potential adverse effects on the breastfed infant from IMLYGIC or from the underlying maternal condition.

Clinical Considerations

Because medicinal products can be found in human milk, a decision should be made whether to discontinue nursing or to discontinue IMLYGIC while nursing.

8.3 Females and Males of Reproductive Potential

No nonclinical or clinical studies were performed to evaluate the effect of IMLYGIC on fertility.

8.4 Pediatric Use

Safety and effectiveness of IMLYGIC have not been established in pediatric patients.

8.5 Geriatric Use

In clinical studies, no overall differences in safety or efficacy were observed between geriatric patients (≥ 65 years old) and younger patients.

8.6 Renal Impairment

No clinical studies have been conducted to evaluate the effect of renal impairment on the pharmacokinetics of IMLYGIC.

8.7 Hepatic Impairment

No clinical studies have been conducted to evaluate the effect of hepatic impairment on the pharmacokinetics of IMLYGIC.

10 OVERDOSAGE

There is no clinical experience with an overdose with IMLYGIC. Doses up to 4 mL at dose strength of 10^8 (100 million) PFU per mL every 2 weeks (maximum cumulative dose of 222.5 x 10^8 PFU) have been administered in clinical studies, with no evidence of dose-limiting toxicity. The maximum dose of IMLYGIC that can be safely administered has not been determined. In the event of a suspected overdose, the patient should be treated symptomatically and supportive measures instituted as required [see Warnings and Precautions (5)].

11 DESCRIPTION

IMLYGIC (talimogene laherparepvec) is a sterile suspension for intralesional injection. IMLYGIC is a live, attenuated HSV-1 that has been genetically modified to express huGM-CSF. The parental virus for IMLYGIC was a primary isolate, which was subsequently altered using recombinant methods to result in gene deletions and insertions.

Each vial contains 1 mL deliverable volume of IMLYGIC at either 1 x 10^6 (1 million) PFU per mL or 1 × 10^8 (100 million) PFU per mL concentrations and the following excipients: di-sodium hydrogen phosphate dihydrate (15.4 mg), sodium dihydrogen phosphate dihydrate (2.44 mg), sodium chloride (8.5 mg), myo-inositol (40 mg), sorbitol (20 mg), and water for injection.

The 10^6 (1 million) PFU per mL vial of IMLYGIC contains a clear to semi-translucent liquid following thaw from its frozen state. The 10^8 (100 million) PFU per mL vial of IMLYGIC contains a semi-translucent to opaque liquid following thaw from its frozen state. The liquid in each vial may contain white, visible, variously shaped, virus-containing particles.

Each vial of IMLYGIC may also contain residual components of VERO cells including DNA and protein and trace quantities of fetal bovine serum.

The product contains no preservative.

12 CLINICAL PHARMACOLOGY

12.1 Mechanism of Action

IMLYGIC has been genetically modified to replicate within tumors and to produce the immune stimulatory protein GM-CSF. IMLYGIC causes lysis of tumors, followed by release of tumor-derived antigens, which together with virally derived GM-CSF may promote an antitumor immune response. However, the exact mechanism of action is unknown.

12.3 Pharmacokinetics

Biodistribution (within the body) and Viral Shedding (excretion/secretion)

IMLYGIC viral DNA levels in various tissues and secretions were determined using a quantitative polymerase chain reaction (qPCR) assay. Infectious IMLYGIC at the injection sites and at some potential herpetic lesions was also quantified using viral infectivity assays.

Nonclinical data

Following repeat intratumoral administration in mice, IMLYGIC DNA was primarily detected in the tumor, blood, spleen, lymph node, liver, heart, and kidney. IMLYGIC DNA was not detected in bone marrow, eyes, lachrymal glands, nasal mucosa, or feces. The highest level of IMLYGIC DNA was found in the injected tumor. IMLYGIC DNA was found in the injected tumor through 84 days and in blood samples through 14 days after the last administration of IMLYGIC.

Clinical data

The biodistribution and shedding of intralesionally administered IMLYGIC were investigated in a clinical study that measured IMLYGIC DNA in blood, urine, injection site, occlusive dressings, oral mucosa, anogenital area, and suspected herpetic lesions. Occlusive dressings samples were collected during treatment. Blood and urine samples were collected during treatment and for up to 30 days after the end of treatment. Injection site, oral mucosa, and anogenital area samples were collected during treatment and for up to 60 days after the end of treatment. Suspected herpetic lesion samples were collected any time a patient experienced lesions of suspected herpetic origin. If the qPCR testing for IMLYGIC DNA was positive, then a TCID50 assay was performed to measure viral infectivity. In the 60 patients with melanoma who received IMLYGIC intralesional injection at a dose and schedule same as the clinical study [see Clinical Studies (14)], data indicate that IMLYGIC DNA was present in all sites during the study (see Table 5).

Table 5. Patients with Detectable DNA During Treatment
Body fluid/Site | Patients with detectable DNA during treatment (n = 60)
Injection site | 60 (100%)
Blood | 59 (98%)
Urine | 19 (32%)
Injection site | 60 (100%)
Occlusive dressing | 48 (80%)
Oral mucosa | 8 (13%)
Anogenital area | 5 (out of 26) [For the anogenital area, 26 patients were tested.]

The proportion of samples and subjects with IMLYGIC DNA was highest during cycle 2 of treatment for the blood, urine, injection site, and occlusive dressings; highest in cycle 1 of treatment for the oral mucosa; and highest in cycles 1 and 2 for the anogenital area. Among patients with detectable IMLYGIC DNA in the blood, urine, oral mucosa and anogenital area, no samples had detectable IMLYGIC DNA 30 days after the end of treatment. For patients with detectable DNA in injected lesions, no samples had detectable IMLYGIC DNA 60 days after the end of treatment.

Overall 3 of 19 patients with lesions of suspected herpetic origin had IMLYGIC DNA present at any time during the study. Of the three subjects who had lesions of suspected herpetic origin that had IMLYGIC DNA detected during the study, none of the suspected lesions were injected with IMLYGIC. None of the subjects with the lesions of the suspected herpetic origin with IMLYGIC DNA had disseminated lesions or received antiviral therapy and these events were non-serious, lasting from 16 days to 4 months. The data suggest that IMLYGIC may cause herpetic lesions in treated patients.

In addition to the presence of IMLYGIC DNA, viral activity was measured in samples that were positive for IMLYGIC DNA from the injection site, occlusive dressings, oral mucosa, anogenital area, and suspected herpetic lesions. No viral activity was detected in samples of the occlusive dressings, oral mucosa, anogenital area, and suspected herpetic lesions. Infectious IMLYGIC virus was detected at the site of injection in 7 (11%) patients at multiple time points in the study; no samples were positive for viral infectivity after cycle 2 or after the end of treatment.

13 NONCLINICAL TOXICOLOGY

13.2 Animal Toxicology and/or Pharmacology

Repeated intratumoral administration at 2 x 10^8 (200 million) PFU per kg (30-fold maximum proposed clinical dose, extrapolated based on body weight) did not demonstrate any adverse effects in immunocompetent mice. Severe combined immunodeficient (SCID) mice administered repeat intratumoral injections of IMLYGIC at a dose of 30-fold maximum proposed clinical dose developed systemic viral infection (viral inclusion bodies or necrosis in enteric neurons in the gastrointestinal tract, adrenal gland, skin, pancreatic islet cells, eye, pineal gland, and brain).

14 CLINICAL STUDIES

The safety and efficacy of intralesional injections of IMLYGIC compared with subcutaneously administered GM-CSF was evaluated in a multicenter, open-label, randomized clinical study in patients with stage IIIB, IIIC, and IV melanoma that was considered to be not surgically resectable. IMLYGIC was injected into cutaneous, subcutaneous, or nodal melanoma lesions and was not injected into visceral lesions. Previous systemic treatment for melanoma was allowed. Patients with active cerebral metastases, bony metastases, extensive visceral disease, primary ocular or mucosal melanoma, evidence of immunosuppression, or receiving treatment with a systemic antiherpetic agent were excluded from the study.

The study included 250 (57%) men and 186 (43%) women. The mean age was 63 (range: 22 to 94) years. Most patients (98%) were white. Seventy percent (70%) of patients had baseline Eastern Cooperative Oncology Group (ECOG) performance status of zero. Seventy percent (70%) of patients had stage IV disease (27% M1a; 21% M1b; and 22% M1c), and 30% had stage III disease. Fifty-three percent (53%) of patients had received prior therapy for melanoma (other than or in addition to surgery, adjuvant therapy, or radiation), and 58% were seropositive for wild-type HSV-1 at baseline.

A total of 436 patients were randomized to receive either IMLYGIC (n = 295) or GM-CSF (n = 141). IMLYGIC was administered by intralesional injection at an initial concentration of 10^6 (1 million) PFU per mL on Day 1, followed by a concentration of 10^8 (100 million) PFU per mL on Day 21 and every 2 weeks thereafter, at a dose of up to 4 mL per visit. GM-CSF was administered subcutaneously in 28-day cycles, i.e., 125 µg/m^2 daily for 14 days followed by 14 days without GM-CSF administration.

Patients were to be treated for at least 6 months or until there were no injectable lesions. During this period, treatment could continue despite an increase in size in existing lesion(s) and/or development of new lesion(s), unless the patient developed intolerable toxicity or the investigator believed that it was in the best interest of the patient to stop treatment or to be given other therapy for melanoma. After 6 months of treatment, patients were to continue treatment until clinically relevant disease progression (i.e., disease progression associated with a decline in performance status and/or alternative therapy was required in the opinion of the investigator), up to 12 months. Patients experiencing a response at 12 months after the start of treatment could continue treatment for up to an additional 6 months, unless there were no remaining injectable lesions or disease progression. All patients were to be followed for survival status for at least 36 months.

The major efficacy outcome was durable response rate (DRR), defined as the percent of patients with complete response (CR) or partial response (PR) maintained continuously for a minimum of 6 months. Tumor responses were determined according to World Health Organization (WHO) response criteria modified to allow patients who developed new lesions or disease progression of existing lesions to continue the treatment and be evaluated later for tumor response.

The DRR was 16.3% in the IMLYGIC arm and 2.1% in the GM-CSF arm in the overall study population. The unadjusted relative risk was 7.6 (95% CI: 2.4, 24.1), with a p-value < 0.0001. The median time to response was 4.1 (range: 1.2 to 16.7) months in the IMLYGIC arm.

There was no statistically significant difference in overall survival (OS) between the IMLYGIC and the GM-CSF arms. The median OS in the overall study population was 22.9 months in the IMLYGIC arm and 19.0 months in the GM-CSF arm (p = 0.116).

16 HOW SUPPLIED/STORAGE AND HANDLING

How Supplied

- IMLYGIC is provided as a sterile frozen suspension in a single-dose, cyclic olefin polymer (COP) plastic resin vial with a chlorobutyl elastomer stopper, aluminum seal, and polypropylene cap in two different presentations:

- Figure 4: Single-dose vial permanently inserted into a clear copolyester plastic sleeve

OR

- Figure 5: Single-dose vial without a clear plastic sleeve

- Each vial contains a retrievable minimal volume of 1 mL.
- The vial cap is color coded:
  - 10^6 (1 million) PFU per mL is light green (NDC 55513-078-01).
  - 10^8 (100 million) PFU per mL is royal blue (NDC 55513-079-01).

Storage and Handling

- Store and transport IMLYGIC at −90°C to −70°C (−130°F to −94°F).
- Protect IMLYGIC from light.
- Store IMLYGIC in the carton until use.
- Thaw IMLYGIC immediately prior to administration [see Dosage and Administration (2.2)].
- Do not draw IMLYGIC into a syringe until immediately prior to administration [see Dosage and Administration (2.2)].

17 PATIENT COUNSELING INFORMATION

Advise patients and/or close contacts to:

- Read the FDA-approved patient labeling (Medication Guide).
- Follow instructions below to prevent viral transmission [see Warnings and Precautions (5.1)]:
  ○ Avoid direct contact with injection sites, dressings, or body fluids of patients.
  ○ Wear gloves when changing dressing.
  ○ Avoid touching or scratching injection sites.
  ○ Keep injection sites covered for at least the first week after each treatment visit or longer if the injection site is weeping or oozing. Replace dressing if it falls off.
  ○ Dispose of used dressings and cleaning materials in household waste in a sealed plastic bag.
- Female patients of childbearing potential should use an effective method of contraception to prevent pregnancy during treatment with IMLYGIC [see Contraindications (4.2) and Use in Specific Populations (8.1)].
- Close contacts who are pregnant or immunocompromised should not change dressings or clean injection sites [see Warnings and Precautions (5.1)].
- In case of accidental exposure to IMLYGIC, clean the exposed area with soap and water and/or a disinfectant. Patients or close contacts with suspected herpetic infections should contact their healthcare provider to evaluate the lesions. Suspected herpetic lesions should be reported to Amgen at 1-855-IMLYGIC (1-855-465-9442); patients or close contacts have the option of follow-up testing for further characterization of the infection [see Warnings and Precautions (5.1) and (5.2)].

IMLYGIC® (talimogene laherparepvec)

Manufactured by:
BioVex LLC, a subsidiary of Amgen Inc.
One Amgen Center Drive
Thousand Oaks, California 91320-1799

Patent: http://pat.amgen.com/Imlygic/

© 2015-2024 Amgen Inc. All rights reserved.
v9

Medication Guide

IMLYGIC® (imm-LY-jik)

(talimogene laherparepvec)

Read the Medication Guide before you start treatment with IMLYGIC and before each IMLYGIC treatment. There may be new information. This Medication Guide does not tell you everything about IMLYGIC. Talk with your healthcare provider if you have any questions about treatment with IMLYGIC.

What is IMLYGIC?

IMLYGIC is a prescription medicine used to treat a type of cancer called melanoma when it is on your skin or in your lymph glands. IMLYGIC is a weakened form of Herpes Simplex Virus Type 1, which is commonly called the cold sore virus. Your healthcare provider will inject IMLYGIC directly into your tumor(s).

IMLYGIC may not help you live longer and may not shrink cancer in your organs (for example, lung or liver).

Who should not get IMLYGIC?

You should not get IMLYGIC if you are pregnant or have a weakened immune system (for example, an immune deficiency, blood or bone marrow cancer, steroid use, or HIV/AIDS).

What should I tell my healthcare provider before I get IMLYGIC?

Before getting IMLYGIC, tell your healthcare provider if you:

- Are taking steroids or other medicines that suppress your immune system.
- Are taking antiviral medicines to treat or prevent herpes, such as acyclovir.
- Have or ever had medical conditions such as:
  ○ HIV infection or AIDS.
  ○ Blood or bone marrow cancer.
  ○ Autoimmune disease.
  ○ Other medical conditions that can weaken your immune system.
- Have close contact with someone who has a weakened immune system or is pregnant.
- Are pregnant or plan to become pregnant.
  ○ IMLYGIC may harm your unborn baby.
  ○ You should not become pregnant during treatment with IMLYGIC.
  ○ Talk to your healthcare provider about effective birth control methods.
- Are breastfeeding or plan to breastfeed.

Tell your healthcare provider about all the medicines you take, including prescription and over-the-counter medicines, vitamins, and herbal supplements. IMLYGIC may affect the way other medicines work and other medicines may affect how IMLYGIC works.

How is IMLYGIC given?

Your healthcare provider will inject IMLYGIC directly into your tumor(s) with a needle and syringe. You will get a second treatment 3 weeks after the first treatment. After that, you will get treatments every 2 weeks for as long as you have tumor(s). You can get treated for 6 months or longer.

Your healthcare provider will decide which tumor(s) to inject and may not inject every one.

It is important to care for the treatment sites properly so that IMLYGIC does not spread to other people. Your healthcare provider will show you how to do this.

What should I avoid while getting IMLYGIC?

IMLYGIC virus can spread to other areas of your body or to your close contacts (household members, caregivers, sex partners, or persons sharing the same bed).

Do the following to avoid spreading IMLYGIC to other areas of your body or to your close contacts:

- Avoid direct contact between your treatment sites, dressings, or body fluids and close contacts (for example, use condoms when engaging in sexual activity, avoid kissing close contacts if either has an open mouth sore).
- Wear gloves while putting on or changing your dressings.
- Keep treatment sites covered with airtight and watertight dressings for at least 1 week after each treatment (or longer if the treatment site is weeping or oozing).
- If the dressing comes loose or falls off, replace it right away with a clean dressing.
- Place all used dressings and cleaning materials in a sealed plastic bag and throw them away in the garbage.
- Do not touch or scratch the treatment sites.

What are possible side effects of IMLYGIC?

The most common side effects of IMLYGIC include:

- Tiredness
- Chills
- Fever
- Nausea
- Flu-like symptoms
- Pain at treatment site

Tell your doctor right away if you get any of the signs and symptoms of herpes infection, including but not limited to:

- Pain, burning, tingling, or blister formation around the mouth, genitals, or any part of the body, near or far from the injection site
- Eye pain, light sensitivity, discharge from the eyes, or blurry vision
- Weakness in arms or legs
- Extreme drowsiness (feeling sleepy)
- Mental confusion

If you think you have a herpes infection, inform your healthcare provider. Life threatening-herpes infection and herpes infection spreading to any part of the body far from the injection site (disseminated herpetic infection) may occur in patients treated with IMLYGIC. If you have any new or worsening symptoms, call your healthcare provider right away. You or your healthcare provider should call Amgen at 1-855-IMLYGIC (1-855-465-9442) for follow-up testing if needed.

These are not all the possible side effects of IMLYGIC. Your healthcare provider can give you more detailed information. Tell your healthcare provider if you have any side effects that bother you or that do not go away. You may report side effects to FDA at 1-800-FDA-1088.

What are the ingredients in IMLYGIC?

Active ingredient: talimogene laherparepvec

Inactive ingredients: di-sodium hydrogen phosphate dihydrate, sodium dihydrogen phosphate dihydrate, sodium chloride, myo-inositol, sorbitol, and water for injection

General information about the safe and effective use of IMLYGIC

This Medication Guide summarizes the most important information about IMLYGIC. Medicines are sometimes prescribed for purposes other than those listed in a Medication Guide. If you would like more information, talk with your healthcare provider. You can ask your healthcare provider for information about IMLYGIC that was written for healthcare professionals.

This Medication Guide has been approved by the U.S. Food and Drug Administration.

IMLYGIC® (talimogene laherparepvec)

Manufactured by:
BioVex LLC, a subsidiary of Amgen Inc.
One Amgen Center Drive
Thousand Oaks, California 91320-1799

Patent: http://pat.amgen.com/Imlygic/

© 2015, 2017, 2022-2024 Amgen Inc. All rights reserved.
Revised: 11/2024
V5

PRINCIPAL DISPLAY PANEL - 10^6 PFU/mL Vial Carton

10^6 PFU/mL Single-Dose Vial

NDC 55513-078-01

AMGEN

talimogene laherparepvec
IMLYGIC®

10^6 Plaque Forming Units (PFU)
per mL

10^6
PFU/mL

For Intralesional Injection Only

Suspension for Injection

No Preservative

Store at -90°C to -70°C (-130°F to
-94°F). Protect from light.

See package insert for full
prescribing information and
instructions for dosage and
administration

Rx Only

PRINCIPAL DISPLAY PANEL - 10^8 PFU/mL Vial Carton

10^8 PFU/mL Single-Dose Vial

NDC 55513-079-01

AMGEN

talimogene laherparepvec
IMLYGIC®

10^8 Plaque Forming Units (PFU)
per mL

10^8
PFU/mL

For Intralesional Injection Only

Suspension for Injection

No Preservative

Store at -90°C to -70°C (-130°F to
-94°F). Protect from light.

See package insert for full prescribing
information and instructions for
dosage and administration

Rx Only